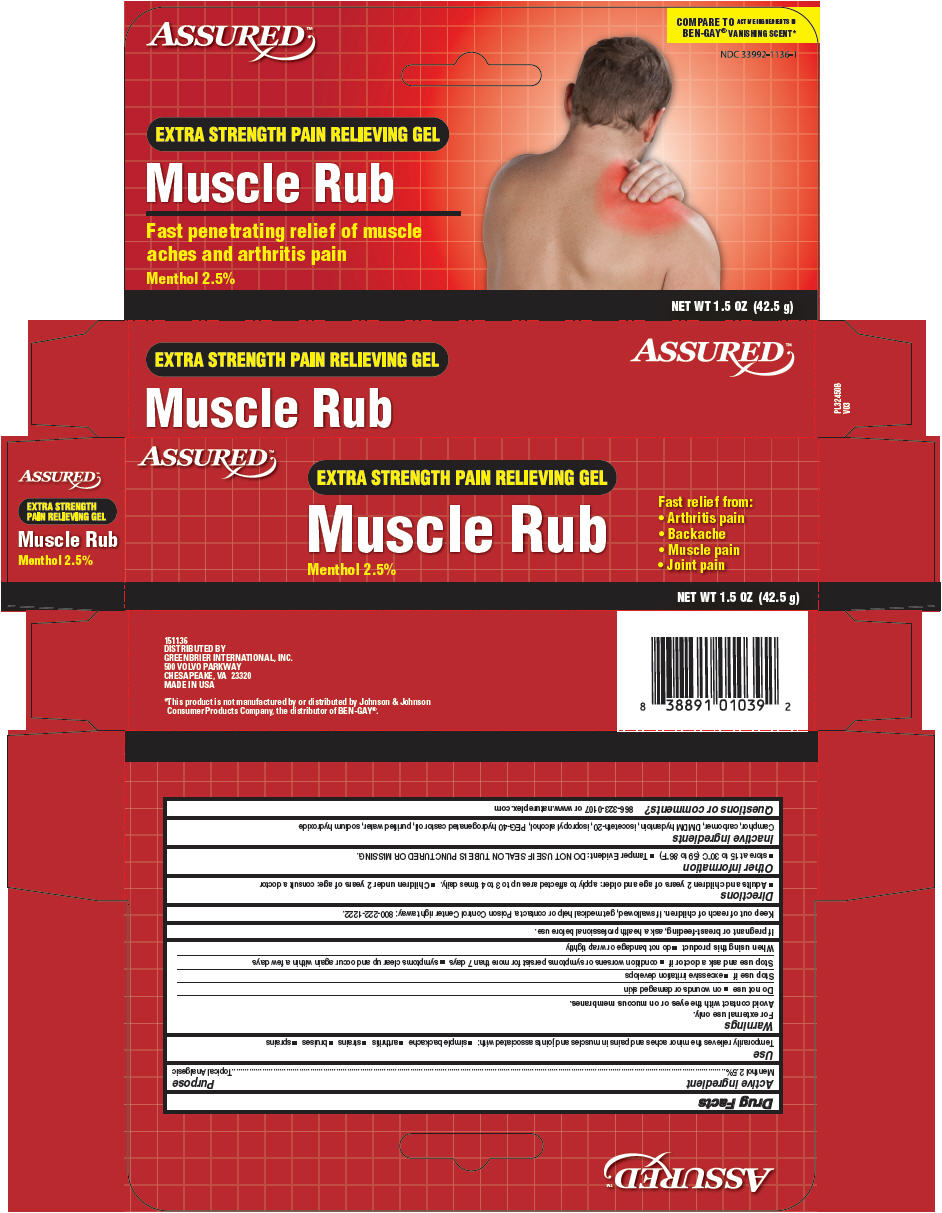 DRUG LABEL: Assured
NDC: 33992-1136 | Form: GEL
Manufacturer: Greenbrier International, Inc.
Category: otc | Type: HUMAN OTC DRUG LABEL
Date: 20171228

ACTIVE INGREDIENTS: MENTHOL, UNSPECIFIED FORM 2.5 g/100 g
INACTIVE INGREDIENTS: CAMPHOR (SYNTHETIC); DMDM HYDANTOIN; ISOPROPYL ALCOHOL; POLYOXYL 40 HYDROGENATED CASTOR OIL; SODIUM HYDROXIDE; WATER

Assured™ Muscle Rub

Drug Facts

Active ingredient

Menthol 2.5%

Purpose

Topical Analgesic

Use

Temporarily relieves the minor aches and pains in muscles and joints associated with:

- simple backache
- arthritis
- strains
- bruises
- sprains

Warnings

For external use only.

Avoid contact with the eyes or on mucous membranes.

Do not use

- on wounds or damaged skin

Stop use if

- excessive irritation develops

Stop use and ask a doctor if

- condition worsens or symptoms persist for more than 7 days
- symptoms clear up and occur again within a few days

When using this product

- do not bandage or wrap tightly

PREGNANCY OR BREAST FEEDING

If pregnant or breast-feeding, ask a health professional before use.

Keep out of reach of children. If swallowed, get medical help or contact a Poison Control Center right away: 800-222-1222.

Directions

- Adults and children 2 years of age and older: apply to affected area up to 3 to 4 times daily.
- Children under 2 years of age: consult a doctor

Other information

- store at 15 to 30°C (59 to 86°F)
- Tamper Evident: DO NOT USE IF SEAL ON TUBE IS PUNCTURED OR MISSING.

Inactive ingredients

Camphor, carbomer, DMDM hydantoin, isoceteth-20, isopropyl alcohol, PEG-40 hydrogenated castor oil, purified water, sodium hydroxide

Questions or comments?

866-323-0107 or www.natureplex.com

DISTRIBUTED BY
GREENBRIER INTERNATIONAL, INC.
500 VOLVO PARKWAY
CHESAPEAKE, VA 23320

PRINCIPAL DISPLAY PANEL - 42.5 g Tube Carton

ASSURED™

EXTRA STRENGTH PAIN RELIEVING GEL

Muscle Rub

Menthol 2.5%

Fast relief from:

- Arthritis pain
- Backache
- Muscle pain
- Joint pain

NET WT 1.5 OZ (42.5 g)